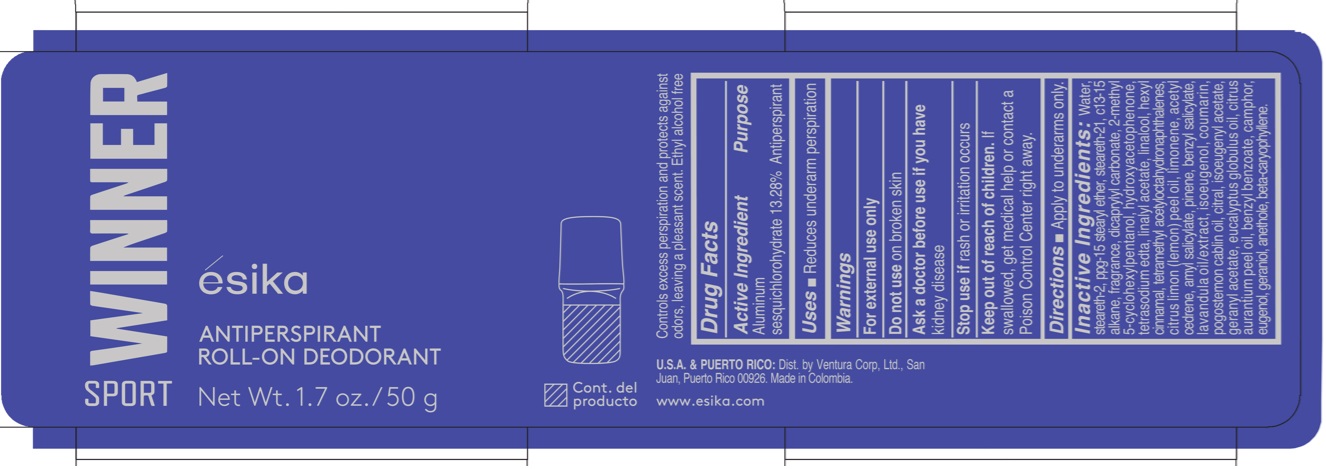 DRUG LABEL: Esika Winner Sport Antiperspirant Roll-on Deodorant
NDC: 14141-365 | Form: EMULSION
Manufacturer: Bel Star S.A.
Category: otc | Type: HUMAN OTC DRUG LABEL
Date: 20241204

ACTIVE INGREDIENTS: ALUMINUM SESQUICHLOROHYDRATE 132.8 mg/1 g
INACTIVE INGREDIENTS: POGOSTEMON CABLIN OIL; GERANYL ACETATE; LAVENDER OIL; EUCALYPTUS GLOBULUS OIL; CAMPHOR (NATURAL); BETA-CARYOPHYLLENE; CITRUS AURANTIUM PEEL OIL; ISOEUGENYL ACETATE; STEARETH-2; BENZYL BENZOATE; EUGENOL; CITRAL; LIMONENE, (+)-; CITRUS LIMON (LEMON) PEEL OIL; GERANIOL; BENZYL SALICYLATE; ISOEUGENOL; COUMARIN; 2-METHYL 5-CYCLOHEXYLPENTANOL; DICAPRYLYL CARBONATE; C13-15 ALKANE; PPG-15 STEARYL ETHER; STEARETH-21; LINALOOL, (+)-; WATER; HYDROXYACETOPHENONE; EDETATE SODIUM; LINALYL ACETATE; HEXYL CINNAMAL; ACETYL CEDRENE; AMYL SALICYLATE; TETRAMETHYL ACETYLOCTAHYDRONAPHTHALENES; PINENE; ANETHOLE

Esika Winner Sport Antiperspirant Roll-on Deodorant

Active Ingredient

Aluminum sesquichlorohydrate 13.28%

Purpose

Antiperspirant

Uses

- reduces underarm perspiration

Warnings

For external use only

Do not use

on broken skin

Ask a doctor before use if you have

kidney disease

Stop use if

rash or irritation occurs

Keep out of reach of children.

If swallowed, get medical help or contact a Poison Control Center right away.

Directions

- Apply to underarms only

Inactive Ingredients

Water, steareth-2, ppg-15 stearyl ether, steareth-21, c13-15 alkane, fragrance, dicaprylyl carbonate, 2-methyl 5-cyclohexylpentanol, hydroxyacetophenone, tetrasodium edta, linalyl acetate, linalool, hexyl cinnamal, tetramethyl acetyloctahydronaphthalenes, citrus limon (lemon) peel oil, limonene, acetyl cedrene, amyl salicylate, pinene, benzyl salicylate, lavandula oil/extract, isoeugenol, coumarin, pogostemon cablin oil, citral, isoeugenyl acetate, geranyl acetate, eucalyptus globulus oil, citrus aurantium peel oil, benzyl benzoate, camphor, eugenol, geraniol, anethole, beta-caryophyllene.

Company Information

Dist. by Ventura Corp, Ltd., San Juan, Puerto Rico 00926.

Made in Colombia.

www.esika.com